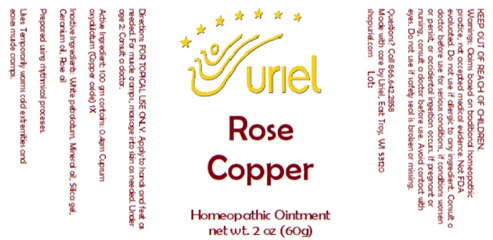 DRUG LABEL: Rose Copper
NDC: 48951-8348 | Form: OINTMENT
Manufacturer: Uriel Pharmacy Inc.
Category: homeopathic | Type: HUMAN OTC DRUG LABEL
Date: 20250107

ACTIVE INGREDIENTS: CUPROUS OXIDE 1 [hp_X]/1 g
INACTIVE INGREDIENTS: PETROLATUM; MINERAL OIL; SILICON DIOXIDE; GERANIUM OIL, ALGERIAN TYPE; ROSE OIL

Rose Copper

INDICATIONS AND USAGE

Directions: FOR TOPICAL USE ONLY.

DOSAGE AND ADMINISTRATION

Apply to hands and feet as needed. For muscle cramps, massage into skin as needed. Under age 2: Consult a doctor.

Active Ingredient: 100 gm contains: 4gm Cuprum oxydulatum (Copper oxide) 1X

INACTIVE INGREDIENT

Inactive Ingredients: White petrolatum, Mineral oil, Silica, Geranium oil, Rose oil

Prepared using rhythmical processes.

PURPOSE

Uses: Temporarily warms cold extremities and eases muscle cramps.

KEEP OUT OF REACH OF CHILDREN.

WARNINGS

Warnings: Claims based on traditional homeopathic practice, not accepted medical evidence. Not FDA evaluated. Do not use if allergic to any ingredient. Consult a doctor before use for serious conditions, if conditions worsen or persist, or accidental ingestion occurs. If pregnant or nursing, consult a doctor before use. Avoid contact with eyes. Do not use if safety seal is broken or missing.

QUESTIONS

Questions? Call 866.642.2858 Made with care by Uriel, East Troy, WI 53120 shopuriel.com Lot: